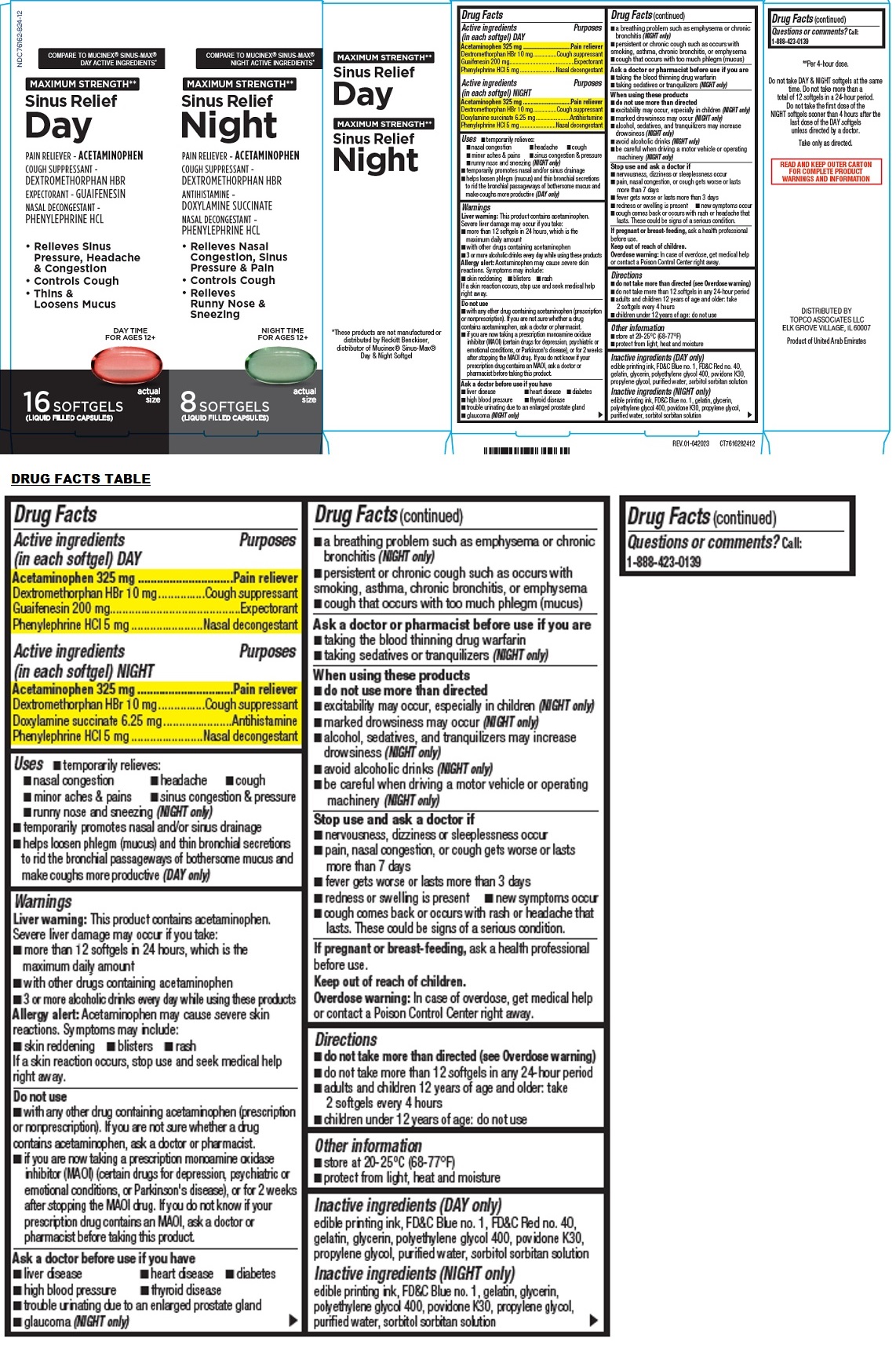 DRUG LABEL: MAXIMUM STRENGTH Sinus Relief
NDC: 76162-824 | Form: KIT | Route: ORAL
Manufacturer: Topco Associates LLC
Category: otc | Type: HUMAN OTC DRUG LABEL
Date: 20231229

ACTIVE INGREDIENTS: ACETAMINOPHEN 325 mg/1 1; DEXTROMETHORPHAN HYDROBROMIDE 10 mg/1 1; GUAIFENESIN 200 mg/1 1; PHENYLEPHRINE HYDROCHLORIDE 5 mg/1 1; ACETAMINOPHEN 325 mg/1 1; DEXTROMETHORPHAN HYDROBROMIDE 10 mg/1 1; DOXYLAMINE SUCCINATE 6.25 mg/1 1; PHENYLEPHRINE HYDROCHLORIDE 5 mg/1 1
INACTIVE INGREDIENTS: FD&C BLUE NO. 1; FD&C RED NO. 40; GELATIN, UNSPECIFIED; GLYCERIN; POLYETHYLENE GLYCOL 400; POVIDONE K30; PROPYLENE GLYCOL; WATER; SORBITOL; SORBITAN; FD&C BLUE NO. 1; GELATIN, UNSPECIFIED; GLYCERIN; POLYETHYLENE GLYCOL 400; POVIDONE K30; PROPYLENE GLYCOL; WATER; SORBITOL; SORBITAN

MAXIMUM STRENGTH Sinus Relief

MAXIMUM STRENGTH** Sinus Relief Day

Drug Facts

Active ingredients (in each softgel) DAY

Acetaminophen 325 mg
Dextromethorphan HBr 10 mg
Guaifenesin 200 mg
Phenylephrine HCl 5 mg

Purposes

Pain reliever
Cough suppressant
Expectorant
Nasal decongestant

Uses

• temporarily relieves:
• nasal congestion • headache • cough • minor aches & pains • sinus congestion & pressure
• temporarily promotes nasal and/or sinus drainage
• helps loosen phlegm (mucus) and thin bronchial secretions to rid the bronchial passageways of bothersome mucus and make coughs more productive.

Warnings

Liver warning: This product contains acetaminophen.
Severe liver damage may occur if you take:
• more than 12 softgels in 24 hours, which is the maximum daily amount
• with other drugs containing acetaminophen
• 3 or more alcoholic drinks every day while using these product

Allergy alert: Acetaminophen may cause severe skin reactions. Symptoms may include: • skin reddening • blisters • rash
If a skin reaction occurs, stop use and seek medical help right away.

Do not use
• with any other drug containing acetaminophen (prescription or nonprescription). If you are not sure whether a drug contains acetaminophen, ask a doctor or pharmacist.
• if you are now taking a prescription monoamine oxidase inhibitor (MAOI) (certain drugs for depression, psychiatric or emotional conditions, or Parkinson's disease), or for 2 weeks after stopping the MAOI drug. If you do not know if your prescription drug contains an MAOI, ask a doctor or pharmacist before taking this product.

Ask a doctor before use if you have
• liver disease • heart disease • diabetes • high blood pressure • thyroid disease • trouble urinating due to enlarged prostate gland • persistent or chronic cough such as occurs with smoking, asthma, chronic bronchitis, or emphysema • cough that occurs with too much phlegm (mucus)

Ask a doctor or pharmacist before use if you are • taking the blood thinning drug warfarin

When using these products • do not use more than directed.

Stop use and ask a doctor if
• nervousness, dizziness or sleeplessness occur
• pain, nasal congestion, or cough gets worse or lasts more than 7 days
• fever gets worse or lasts more than 3 days
• redness or swelling is present • new symptoms occur
• cough comes back or occurs with rash or headache that lasts. These could be signs of a serious condition.

If pregnant or breast-feeding, ask a health professional before use.

Keep out of reach of children.
Overdose warning: In case of overdose, get medical help or contact a Poison Control Center right away.

Directions

• do not take more than directed (see Overdose warning)
• do not take more than 12 softgels in any 24-hour period
• adults and children 12 years of age and older: take 2 softgels every 4 hours
• children under 12 years of age: do not use

Other information

• store at 20-25°C (68-77°F)
• protect from light, heat and moisture

Inactive ingredients

edible printing ink, FD&C Blue no. 1, FD&C Red no. 40, gelatin, glycerin, polyethylene glycol 400, povidone K30, propylene glycol, purified water, sorbitol sorbitan solution

Questions or comments?

Call: 1-888-423-0139

MAXIMUM STRENGTH** Sinus Relief Night

Drug Facts

Active ingredients (in each softgel) NIGHT

Acetaminophen 325 mg
Dextromethorphan HBr 10 mg
Doxylamine succinate 6.25 mg
Phenylephrine HCl 5 mg

Purposes

Pain reliever
Cough suppressant
Antihistamine
Nasal decongestant

Uses

• temporarily relieves:
• nasal congestion • headache • cough • minor aches & pains • sinus congestion & pressure • runny nose and sneezing
• temporarily promotes nasal and/or sinus drainage

Warnings

Liver warning: This product contains acetaminophen.
Severe liver damage may occur if you take:
• more than 12 softgels in 24 hours, which is the maximum daily amount
• with other drugs containing acetaminophen
• 3 or more alcoholic drinks every day while using these products

Allergy alert: Acetaminophen may cause severe skin reactions. Symptoms may include: • skin reddening • blisters • rash
If a skin reaction occurs, stop use and seek medical help right away.

Do not use
• with any other drug containing acetaminophen (prescription or nonprescription). If you are not sure whether a drug contains acetaminophen, ask a doctor or pharmacist.
• if you are now taking a prescription monoamine oxidase inhibitor (MAOI) (certain drugs for depression, psychiatric or emotional conditions, or Parkinson's disease), or for 2 weeks after stopping the MAOI drug. If you do not know if your prescription drug contains an MAOI, ask a doctor or pharmacist before taking this product.

Ask a doctor before use if you have
• liver disease • heart disease • diabetes • high blood pressure • thyroid disease • trouble urinating due to enlarged prostate gland • glaucoma • a breathing problem such as emphysema or chronic bronchitis • persistent or chronic cough such as occurs with smoking, asthma, chronic bronchitis, or emphysema • cough that occurs with too much phlegm (mucus)

Ask a doctor or pharmacist before use if you are • taking the blood thinning drug warfarin • taking sedatives or tranquilizers

When using these products
• do not use more than directed
• excitability may occur, especially in children
• marked drowsiness may occur
• alcohol, sedatives, and tranquilizers may increase drowsiness
• avoid alcoholic drinks
• be careful when driving a motor vehicle or operating machinery

Stop use and ask a doctor if
• nervousness, dizziness or sleeplessness occur
• pain, nasal congestion, or cough gets worse or lasts more than 7 days
• fever gets worse or lasts more than 3 days
• redness or swelling is present • new symptoms occur
• cough comes back or occurs with rash or headache that lasts. These could be signs of a serious condition.

If pregnant or breast-feeding, ask a health professional before use.

Keep out of reach of children.
Overdose warning: In case of overdose, get medical help or contact a Poison Control Center right away.

Directions

• do not take more than directed (see Overdose warning)
• do not take more than 12 softgels in any 24-hour period
• adults and children 12 years of age and older: take 2 softgels every 4 hours
• children under 12 years of age: do not use

Other information

• store at 20-25°C (68-77°F)
• protect from light, heat and moisture

Inactive ingredients

edible printing ink, FD&C Blue no. 1, gelatin, glycerin, polyethylene glycol 400, povidone K30, propylene glycol, purified water, sorbitol sorbitan solution

Questions or comments?

Call: 1-888-423-0139

COMPARE TO MUCINEX® SINUS-MAX® DAY ACTIVE INGREDIENTS*

COMPARE TO MUCINEX® SINUS-MAX® NIGHT ACTIVE INGREDIENTS*

DAY TIME FOR AGES 12+
NIGHT TIME FOR AGES 12+

*These products are not manufactured or distributed by Reckitt Benckiser, distributor of Mucinex® Sinus-Max® Day & Night Softgel

**Per 4-hour dose.

Do not take DAY & NIGHT softgels at the same time. Do not take more than a total of 12 softgels in a 24-hour period. Do not take the first dose of the NIGHT softgels sooner than 4 hours after the last dose of the DAY softgels unless directed by a doctor.

Take only as directed.

READ AND KEEP OUTER CARTON FOR COMPLETE PRODUCT WARNINGS AND INFORMATION

DISTRIBUTED BY
TOPCO ASSOCIATES LLC
ELK GROVE VILLAGE, IL 60007

Product of United Arab Emirates

REV.01-042023 CT7616282412